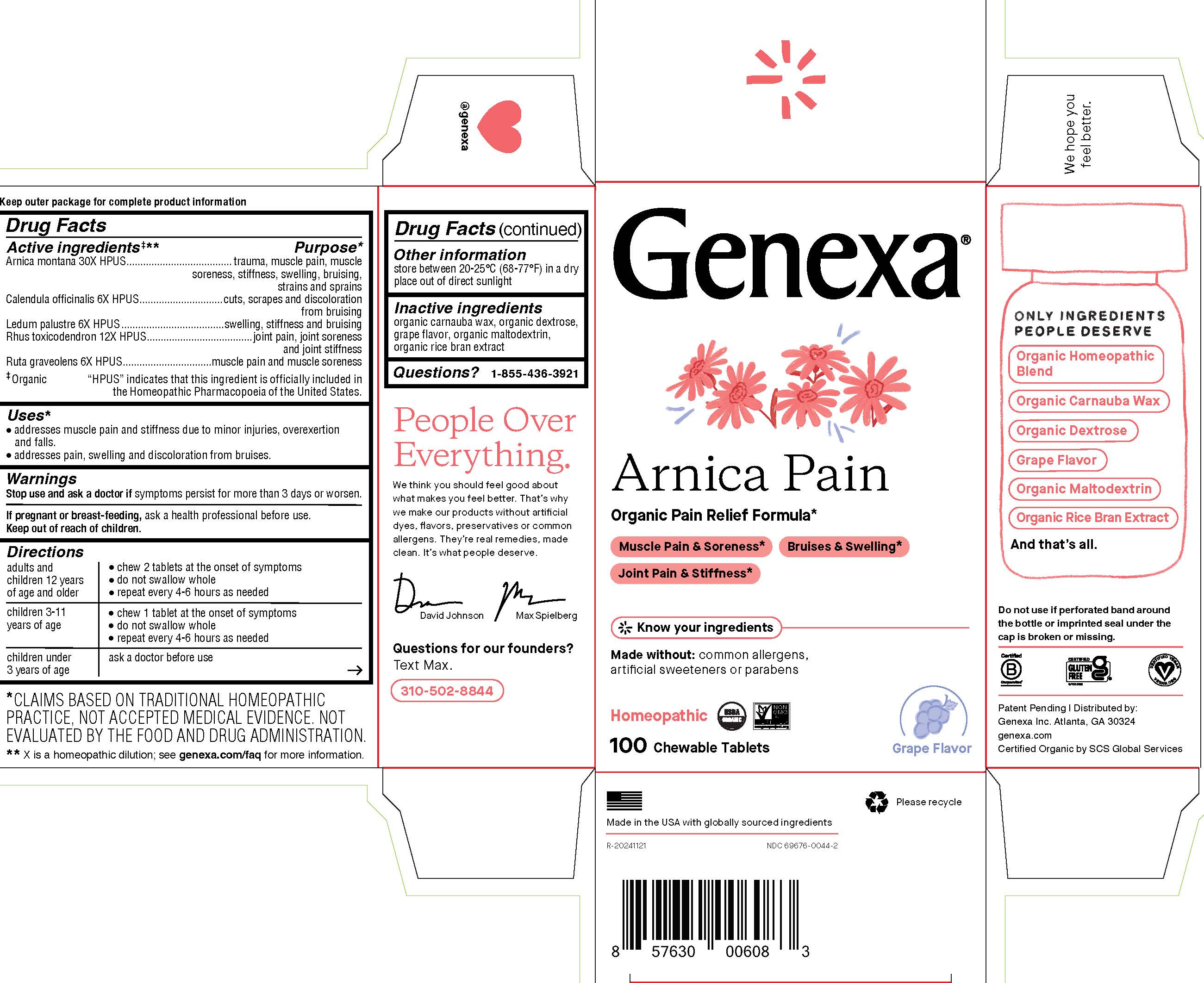 DRUG LABEL: Genexa Arnica Pain
NDC: 69676-0044 | Form: TABLET, CHEWABLE
Manufacturer: Genexa Inc.
Category: homeopathic | Type: HUMAN OTC DRUG LABEL
Date: 20250402

ACTIVE INGREDIENTS: TOXICODENDRON PUBESCENS LEAF 12 [hp_X]/1 1; ARNICA MONTANA 30 [hp_X]/1 1; CALENDULA OFFICINALIS FLOWERING TOP 6 [hp_X]/1 1; LEDUM PALUSTRE TWIG 6 [hp_X]/1 1; RUTA GRAVEOLENS FLOWERING TOP 6 [hp_X]/1 1
INACTIVE INGREDIENTS: CARNAUBA WAX; MALTODEXTRIN; RICE BRAN; DEXTROSE

ARNICA PAIN

Drug Facts

Active ingredients‡**

Arnica montana 30X HPUS

Calendula officinalis 6X HPUS

Ledum palustre 6X HPUS

Rhus toxicodendron 12X HPUS

Ruta graveolens 6X HPUS

‡ Organic

"HPUS" indicates that this ingredient is officially included in the Homeopathic Pharmacopoeia of the United States.

Purpose*

trauma, muscle pain, muscle soreness, stiffness, swelling, bruising, strains and sprains

cuts, scrapes and discoloration from bruising

swelling, stiffness and bruising

joint pain, joint soreness and joint stiffness

muscle pain and muscle soreness

Uses*

- addresses muscle pain and stiffness due to minor injuries, overexertion and falls.
- addresses pain, swelling and discoloration from bruises.

Warnings

Stop use and ask a doctorif symptoms persist for more than 3 days or worsen.

PREGNANCY OR BREAST FEEDING

If pregnant or breastfeeding, ask a health professional before use.

Keep out of reach of children.

Directions

adults and children 12 years of age and older | - chew 2 tablets at the onset of symptoms - do not swallow whole - repeat every 4-6 hours as needed
children 3-11 years of age | - chew 1 tablet at the onset of symptoms - do not swallow whole - repeat every 4-6 hours as needed
children under 3 years of age | ask a doctor before use

Other information

store between 20-25° C (68-77° F) in a dry place out of direct sunlight

Inactive ingredients

organic carnauba wax, organic dextrose, grape flavor, organic maltodextrin, organic rice bran extract

Questions?

1-855-436-3921

*CLAIMS BASED ON TRADITIONAL HOMEOPATHIC PRACTICE, NOT ACCEPTED MEDICAL EVIDENCE. NOT EVALUATED BY THE FOOD AND DRUG ADMINISTRATION.

** X is a homeopathic dilution; see genexa.com/faq for more information.

Do not use if perforated band around the bottle or imprinted seal under the cap is broken or missing.

Patent Pending | Distributed by:

Genexa Inc. Atlanta, GA 30324

genexa.com

Certified Organic by SCS Global Services

Made in the USA with globally sourced ingredients

NDC 69676-0044-2

PACKAGE LABEL

Genexa®

Arnica Pain

Organic Pain Relief Formula*

Muscle Pain & Soreness*

Bruises & Swelling*

Joint Pain & Stiffness*

Made without: common allergens, artificial dyes, or parabens

Homeopathic

100 Chewable Tablets

Grape Flavor